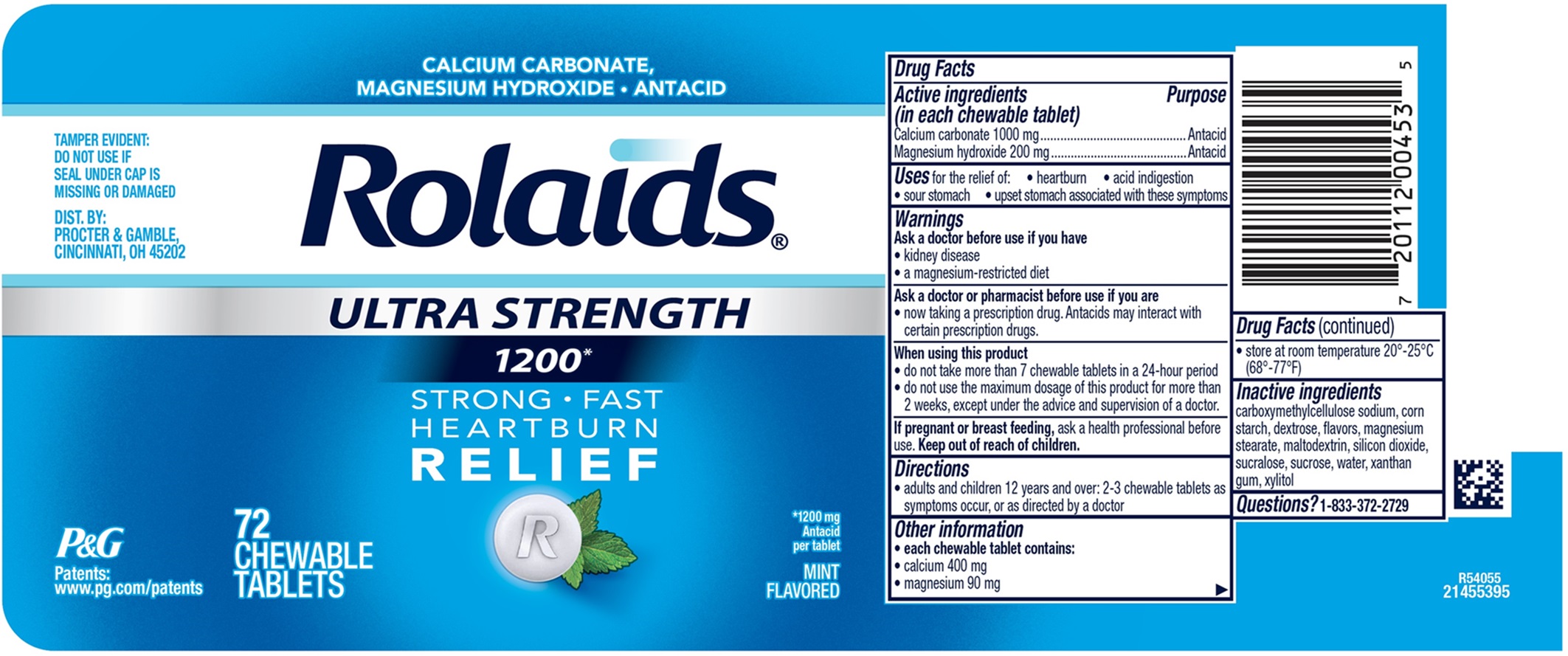 DRUG LABEL: Rolaids ULTRA STRENGTH 1200
NDC: 84126-325 | Form: TABLET, CHEWABLE
Manufacturer: THE PROCTER & GAMBLE MANUFACTURING COMPANY
Category: otc | Type: HUMAN OTC DRUG LABEL
Date: 20251202

ACTIVE INGREDIENTS: CALCIUM CARBONATE 1000 mg/1 1; MAGNESIUM HYDROXIDE 200 mg/1 1
INACTIVE INGREDIENTS: DEXTROSE; MAGNESIUM STEARATE; SILICON DIOXIDE; SUCRALOSE; SUCROSE; STARCH, CORN; WATER; XANTHAN GUM; XYLITOL; MALTODEXTRIN

Rolaids ULTRA STRENGTH 1200

Drug Facts

Active ingredients

(in each chewable tablet)
Calcium carbonate 1000 mg
Magnesium hydroxide 200 mg

Purposes

Antacid

Antacid

Uses

for the relief of:

- heartburn
- acid indigestion
- sour stomach
- upset stomach associated with these symptoms

Warnings

Ask a doctor before use if you have

- kidney disease
- a magnesium-restricted diet

Ask a doctor or pharmacist before use if you are

- now taking a prescription drug. Antacids may interact with certain prescription drugs.

When using this product

- do not take more than 7 tablets in a 24-hour period
- do not use the maximum dosage for more than 2 weeks, except under the advice and supervision of a doctor

Directions

- adults and children 12 years and over: 2-3 chewable tablets as symptoms occur, or as directed by a doctor

Other information

- each chewable tablet contains:
- calcium 400 mg
- magnesium 90 mg
- store at room temperature 20º -25°C (68º - 77°F)

Inactive ingredients

carboxymethylcellulose sodium, corn starch, dextrose, flavors, magnesium stearate, maltodextrin, silicon dioxide, sucralose, sucrose, water, xanthan gum, xylitol

Questions?

1-833-372-2729

TAMPER EVIDENT: DO NOT USE IF SEAL UNDER CAP IS MISSING OR DAMAGED

DIST. BY: PROCTER & GAMBLE, CINCINNATI, OH 45202

PRINCIPAL DISPLAY PANEL

CALCIUM CARBONATE, MAGNESIUM HYDROXIDE • ANTACID

Rolaids

ULTRA STRENGTH

1200*

STRONG • FAST

HEARTBURN

RELIEF

*1200 mg Antacid per tablet

MINT FLAVORED

72 CHEWABLE TABLETS